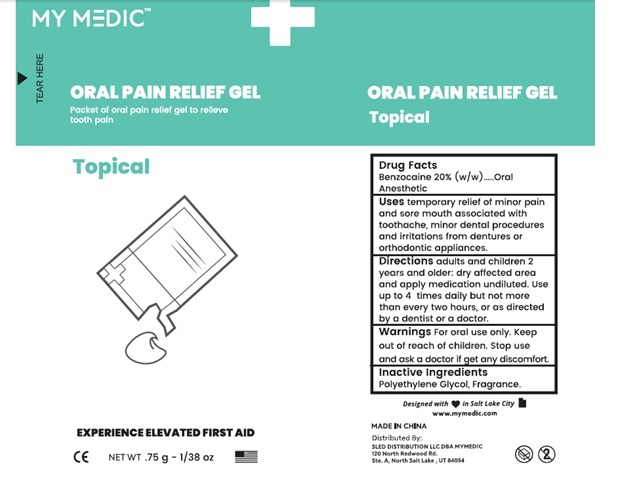 DRUG LABEL: Oral Pain Relief Gel
NDC: 81417-001 | Form: GEL
Manufacturer: Sled Distribution, LLC
Category: otc | Type: HUMAN OTC DRUG LABEL
Date: 20240115

ACTIVE INGREDIENTS: BENZOCAINE 200 mg/1 g
INACTIVE INGREDIENTS: POLYETHYLENE GLYCOL, UNSPECIFIED

81417-001 MY MEDIC ORAL PAIN RELIEF GEL

Active ingredient

Benzocaine 20% (w/w)

Purpose

Oral anesthetic

INDICATIONS AND USAGE

Uses temporary relief of minor pain and sore mouth associated with toothache, minor dental procedures and irritations from dentures or orthodontic appliances.

Warnings

For oral use only.

Stop use and ask a doctor if get any discomfort.

Keep out of reach of children.

DOSAGE AND ADMINISTRATION

Directions adults and children 2 years and older: dry affected area and apply medication undiluted. Use up to 4 times daily but not more than every two hours, or as directed by a dentist or a doctor.

Inactive ingredients

Polyethylene Glycol, Fragrance